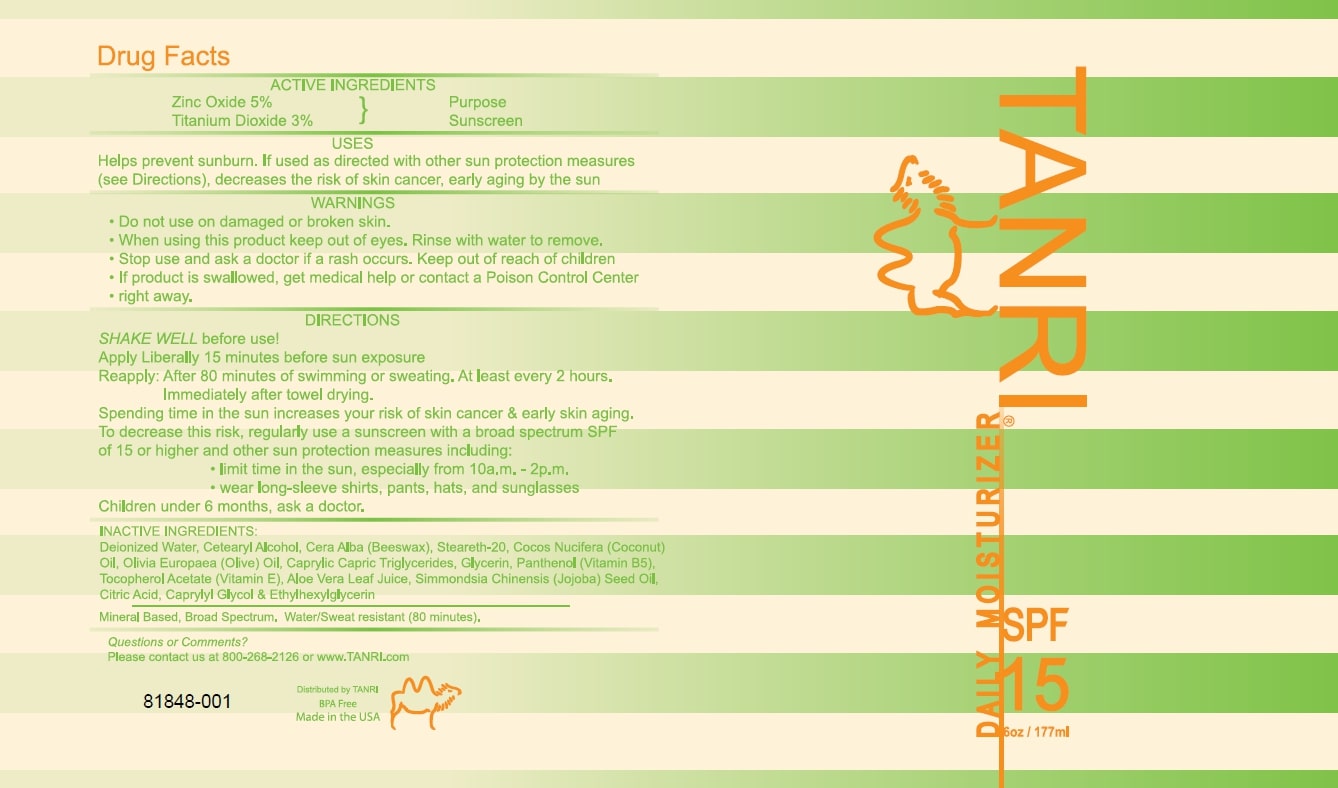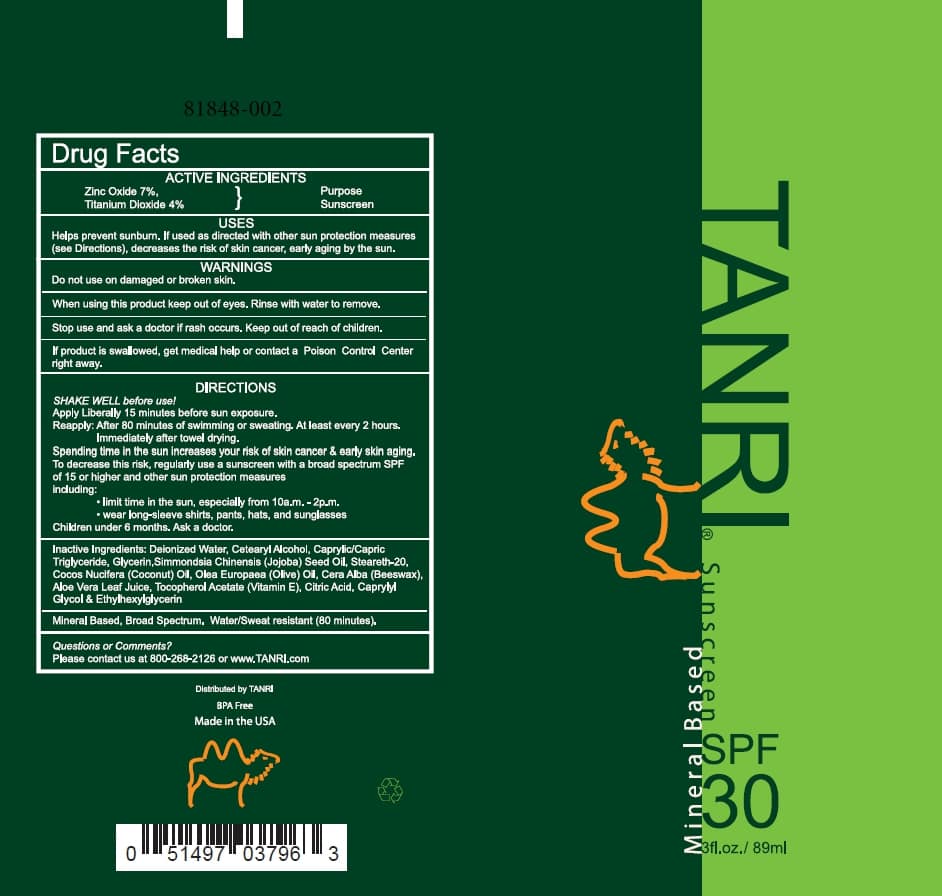 DRUG LABEL: TANRI Sunscreen SPF15
NDC: 81848-001 | Form: LOTION
Manufacturer: Valley Cash & Carry, Inc.
Category: otc | Type: HUMAN OTC DRUG LABEL
Date: 20210427

ACTIVE INGREDIENTS: ZINC OXIDE 5 g/100 mL; TITANIUM DIOXIDE 3 g/100 mL
INACTIVE INGREDIENTS: WATER; SYNTHETIC BEESWAX; COCOS NUCIFERA WHOLE; OLEA EUROPAEA (OLIVE) OIL UNSAPONIFIABLES; CAPRYLIC/CAPRIC/LAURIC TRIGLYCERIDE; GLYCERIN; PANTHENOL; ALPHA-TOCOPHEROL ACETATE; ALOE VERA LEAF; JOJOBA OIL; CITRIC ACID ACETATE; caprylyl glycol; ETHYLHEXYLGLYCERIN

TANRI Mineral Based Sunscreen SPF30

ACTIVE INGREDIENTS:
Zinc Oxide,
Titanium Dioxide

Purpose: Sunscreen

Keep out of reach of children.

Children under 6 months, ask a doctor.

Uses

Helps prevent sunburn. If used as directed with other sun protection measures(see Directions), decreases the risk of skin cancer, early aging by the sun

WARNINGS
• Do not use on damaged or broken skin.
• When using this product keep out of eyes. Rinse with water to remove.
• Stop use and ask a doctor if a rash occurs. Keep out of reach of children
• If product is swallowed, get medical help or contact a Poison Control Center
right away.

Directions

SHAKE WELL before use!
Apply Liberally 15 minutes before sun exposure
Reapply: After 80 minutes of swimming or sweating. At least every 2 hours.
Immediately after towel drying.
Spending time in the sun increases your risk of skin cancer & early skin aging.
To decrease this risk, regularly use a sunscreen with a broad spectrum SPF
of 15 or higher and other sun protection measures including:
• limit time in the sun, especially from 10a.m. - 2p.m.
• wear long-sleeve shirts, pants, hats, and sunglasses
Children under 6 months, ask a doctor.

INACTIVE INGREDIENTS:

Deionized Water, Cetearyl Alcohol, Cera Alba (Beeswax), Steareth-20, Cocos Nucifera (Coconut) Oil, Olivia Europaea (Olive) Oil, Caprylic Capric Triglycerides, Glycerin, Panthenol (Vitamin B5), Tocopherol Acetate (Vitamin E), Aloe Vera Leaf Juice, Simmondsia Chinensis (Jojoba) Seed Oil, Citric Acid, Caprylyl Glycol & Ethylhexylglycerin Mineral Based, Broad Spectrum. Water/Sweat resistant (80 minutes).

PACKAGE LABEL

Tanri SPF15 Mineral Sunscreen - 6oz/177ml

NDC: 81848-001

Tanri SPF30 Mineral Sunscreen - 3oz/89ml

NDC: 81848-002